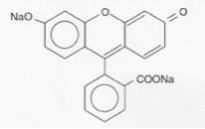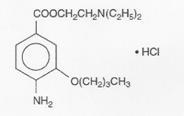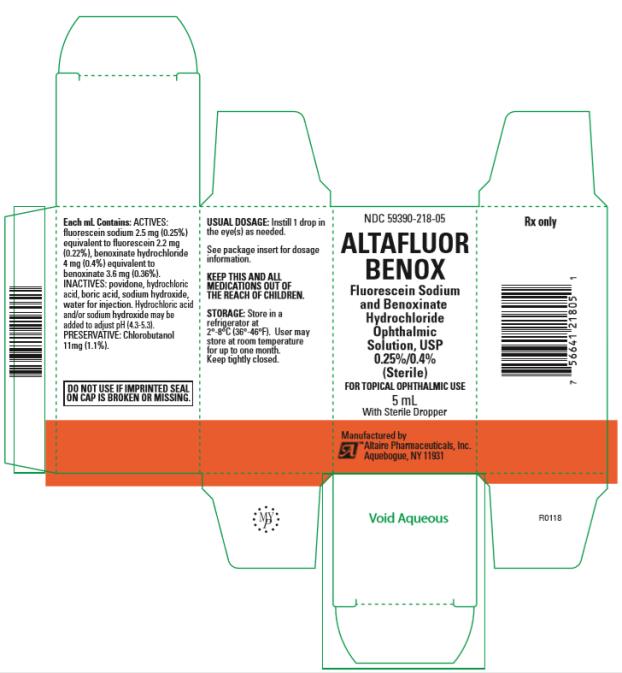 DRUG LABEL: ALTAFLUOR
NDC: 59390-218 | Form: SOLUTION
Manufacturer: Altaire Pharmaceuticals Inc.
Category: prescription | Type: HUMAN PRESCRIPTION DRUG LABEL
Date: 20171206

ACTIVE INGREDIENTS: FLUORESCEIN SODIUM 2.5 mg/1 mL; BENOXINATE HYDROCHLORIDE 4 mg/1 mL
INACTIVE INGREDIENTS: CHLOROBUTANOL 11 mg/1 mL; POVIDONE; HYDROCHLORIC ACID; BORIC ACID; SODIUM HYDROXIDE; WATER

HIGHLIGHTS OF PRESCRIBING INFORMATION

These highlights do not include all the information needed to use ALTAFLUOR BENOX safely and effectively. See full prescribing information for ALTAFLUOR BENOX.
Altafluor Benox (fluorescein sodium and benoxinate hydrochloride ophthalmic solution) 0.25%/0.4% for topical ophthalmic use
Initial U.S. Approval: 2017

1 INDICATIONS AND USAGE

Altafluor Benox (fluorescein sodium and benoxinate hydrochloride ophthalmic solution) 0.25%/0.4% is a combination disclosing agent and local ester anesthetic indicated for procedures requiring a disclosing agent in combination with a topical ophthalmic anesthetic. (1)

2 DOSAGE AND ADMINISTRATION

Instill 1 to 2 drops topically in the eye as needed to achieve adequate anesthesia. (2)

3 DOSAGE FORMS AND STRENGTHS:

Ophthalmic solution containing fluorescein sodium 2.5 mg/mL (0.25%) and benoxinate hydrochloride 4 mg/mL (0.4%). (3)

4 CONTRAINDICATIONS:

Known hypersensitivity to any component of this product. (4)

5 WARNINGS AND PRECAUTIONS

- Corneal toxicity: Prolonged use or abuse may lead to corneal epithelial toxicity and manifest as epithelial defects which may progress to permanent corneal damage. (5.1)
- Corneal injury: Patients should not touch the eye for approximately 20 minutes after using anesthetic as accidental injuries can occur due to insensitivity of the eye. (5.2)

6 ADVERSE REACTIONS

The most common ocular adverse events are: stinging, burning and conjunctival redness. (6)

To report SUSPECTED ADVERSE REACTIONS, contact Altaire Pharmaceuticals, Inc., at 1-800-258-2471 or FDA at 1-800-FDA-1088 or www.fda.gov/medwatch.

FULL PRESCRIBING INFORMATION

1 INDICATIONS AND USAGE

Altafluor Benox (fluorescein sodium and benoxinate hydrochloride ophthalmic solution) 0.25%/0.4% is indicated for ophthalmic procedures requiring a disclosing agent in combination with a topical ophthalmic anesthetic agent.

2 DOSAGE AND ADMINISTRATION

Instill 1 to 2 drops of Altafluor Benox in the eye as needed.

3 DOSAGE FORMS AND STRENGTHS:

Altafluor Benox is a yellow to orange-red ophthalmic solution containing fluorescein sodium 2.5 mg/mL (0.25%) and benoxinate hydrochloride 4 mg/mL (0.4%).

4 CONTRAINDICATIONS:

Altafluor Benox is contraindicated in patients with known hypersensitivity to any component of this product.

5 WARNINGS AND PRECAUTIONS

5.1 Corneal Toxicity

Prolonged use or abuse may lead to corneal epithelial toxicity which may manifest as epithelial defects and progress to permanent corneal opacification with accompanying visual loss.

5.2 Corneal Injury Due to Insensitivity

Patient should not touch the eye for approximately 20 minutes after using this anesthetic as accidental injuries can occur due to insensitivity of the eye.

6 ADVERSE REACTIONS

The following ocular adverse reactions are described elsewhere in the labeling:

- Corneal Toxicity [see Warnings and Precautions (5.1)]
- Corneal Injury due to Insensitivity [see Warnings and Precautions (5.2)]

The following adverse reactions have been identified following use of fluorescein sodium and benoxinate hydrochloride ophthalmic solution 0.25% / 0.4%: ocular hyperemia, burning, stinging, eye irritation, blurred vision and punctate keratitis. Because these reactions were reported voluntarily from a population of uncertain size, it is not always possible to reliably estimate their frequency or establish a causal relationship to drug exposure.

8 USE IN SPECIFIC POPULATIONS

8.1 Pregnancy

Risk Summary

There are no available data on the use of Altafluor Benox in pregnant women to inform any drug associated risk. Adequate animal reproduction studies have not been conducted with fluorescein sodium and/or benoxinate hydrochloride. Altafluor Benox should be given to a pregnant woman only if clearly needed.

8.2 Lactation

Risk Summary

There are no data on the presence of fluorescein sodium or benoxinate hydrochloride in human milk after ocular administration of Altafluor Benox, the effects on the breastfed infant, or the effects on milk production.

The developmental and health benefits of breastfeeding should be considered, along with the mother’s clinical need for Altafluor Benox and any potential adverse effects on the breastfed infant from Altafluor Benox.

8.4 Pediatric Use

The safety and effectiveness of Altafluor Benox have been established for pediatric patients. Use of Altafluor Benox is supported in pediatric patients by evidence from adequate and well controlled studies.

8.5 Geriatric Use

No overall differences in safety or effectiveness have been observed between elderly and younger patients.

11 DESCRIPTION

Altafluor Benox (fluorescein sodium and benoxinate hydrochloride ophthalmic solution) 0.25%/0.4% is a sterile disclosing agent in combination with a short-acting ester anesthetic for topical ophthalmic use.

Fluorescein sodium is represented by the following structural formula:

C20H10Na2O5 Mol. Wt. 376.27

Chemical Name: Spiro [isobenzofuran-1 (3H),9’-9[9H] xanthene]-3-one, 3’,6’ dihydroxy, disodium salt.

Benoxinate hydrochloride is represented by the following structural formula:

C17H28N2O3 • HCl Mol. Wt. 344.88

Chemical Name: 2-(Diethylamino) etyl 4-amino-3-butoxybenzoate monohydrochloride.

Each mL contains: Actives: fluorescein sodium 2.5 mg (0.25%) equivalent to fluorescein 2.2 mg (0.22%), benoxinate hydrochloride 4 mg (0.4%) equivalent to benoxinate 3.6 mg (0.36%); Inactives: povidone, hydrochloric acid, boric acid, sodium hydroxide, water for injection. Hydrochloric acid and/or sodium hydroxide may be added to adjust pH (4.3 – 5.3). Preservative: chlorobutanol 11mg (1.1%).

12. CLINICAL PHARMACOLOGY

This product is the combination of a disclosing agent with a rapidly acting ester anesthetic of short duration.

12.2 Pharmacodynamics

Maximal corneal anesthesia usually occurs in about 5-45 seconds and lasts about 20 minutes after single administration. The anesthetic effect may be extended by subsequent administration 10-20 minutes after the last administration.

13 NONCLINICAL TOXICOLOGY

13.1 Carcinogenesis, Mutagenesis, Impairment of Fertility

Long-term studies to evaluate the carcinogenic potential of Altafluor Benox have not been conducted.

14 CLINICAL STUDIES

Controlled clinical studies in adults and pediatric patients have demonstrated that topical administration of fluorescein sodium and benoxinate hydrochloride ophthalmic solution 0.25%/0.4% enables visualization and corneal anesthesia sufficient to enable applanation tonometry, tear fluid dynamics evaluation and short conjunctival and corneal procedures. Maximal corneal anesthesia usually occurs in about 5-45 seconds and lasts about 20 minutes after single administration.

16 HOW SUPPLIED/STORAGE AND HANDLING

Altafluor Benox (fluorescein sodium and benoxinate hydrochloride ophthalmic solution) 0.25%/0.4% is a sterile, yellow to orange-red solution supplied in a 5 mL glass bottle with a sterilized dropper.

NDC #59390-218-05

Storage: Store in refrigerator at 2° to 8°C (36° to 46°F). After opening, Altafluor Benox can be stored up to one month if stored at room temperature or until the expiration date on the bottle if stored in refrigerated conditions. Keep tightly closed.

17 PATIENT COUNSELING INFORMATION

Accidental Injury Precaution

Advise patients not to touch their eyes for approximately 20 minutes after application. Their eyes will be insensitive due to the effect of the anesthetic, and care should be taken to avoid accidental injuries.

Rev. 12/2017

Manufactured by:
ALTAIRE Pharmaceuticals, Inc.
Aquebogue, NY 11931

PRINCIPAL DISPLAY PANEL

NDC 59390-218-05
ALTAFLUOR
BENOX
Fluorescein Sodium and
Benoxinate Hydrochloride
Ophthalmic Solution, USP
0.25%/0.4%
(Sterile)
5 mL
Rx Only